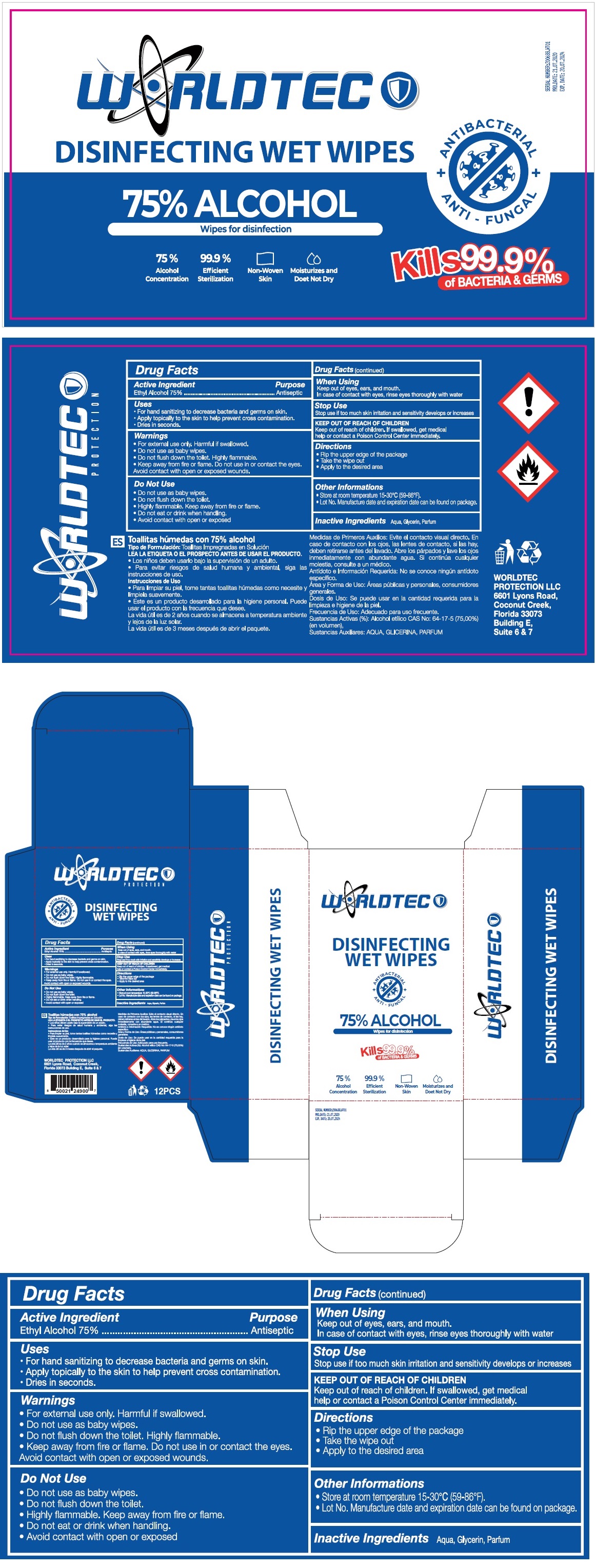 DRUG LABEL: WORLDTEC DISINFECTING WET WIPES 75% ALCOHOL
NDC: 76725-014 | Form: CLOTH
Manufacturer: MAKYAJ KOZMETIK INSAAT SANAYI VE TICARET LIMITED SIRKETI
Category: otc | Type: HUMAN OTC DRUG LABEL
Date: 20200918

ACTIVE INGREDIENTS: ALCOHOL 75 g/100 g
INACTIVE INGREDIENTS: WATER; GLYCERIN

WORLDTEC DISINFECTING WET WIPES 75% ALCOHOL

Active Ingredient

Ethyl Alcohol 75%

Purpose

Antiseptic

Uses

• For hand sanitizing to decrease bacteria and germs on skin.

• Apply topically to the skin to help prevent cross contamination.

• Dries in seconds.

Warnings

• For external use only. Harmful if swallowed.

• Do not use as baby wipes.

• Do not flush down the toilet. Highly flammable.

• Keep away from fire or flame. Do not use in or contact the eyes.

Avoid contact with open or exposed wounds.

Do Not Use

• Do not use as baby wipes.

• Do not flush down the toilet.

• Highly flammable. Keep away from fire or flame.

• Do not eat or drink when handling.

• Avoid contact with open or exposed

When Using

Keep out of eyes, ears, and mouth.

In case of contact with eyes, rinse eyes thoroughly with water

Stop Use

Stop use if too much skin irritation and sensitivity develops or increases

Keep out of reach of children. If swallowed, get medical help or contact a Poison Control Center immediately.

Directions

• Rip the upper edge of the package

• Take the wipe out

• Apply to the desired area

Other Informations

• Store at room temperature 15-30℃ (59-86°F).

• Lot No. Manufacture date and expiration date can be found on package.

Inactive Ingredients Aqua, Glycerin, Parfum

ANTIBACTERIAL

ANTI - FUNGAL

Wipes for disinfection

Kills 99.9% of BACTERIA & GERMS

99.9% Efficient Sterilization

Non-Woven Skin

Moisturizes and Does Not Dry

WORLDTEC PROTECTION LLC

6601 Lyons Road, Coconut Creek,

Florida 33073 Building E, Suite 6 & 7